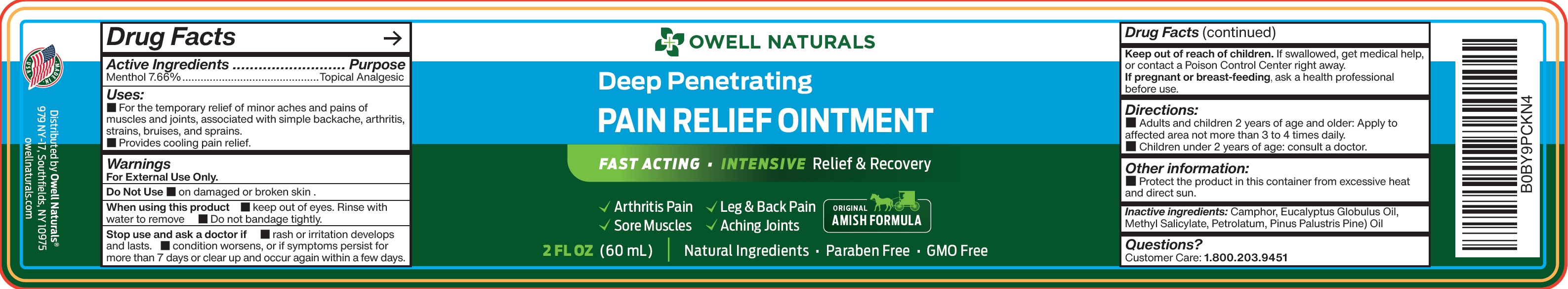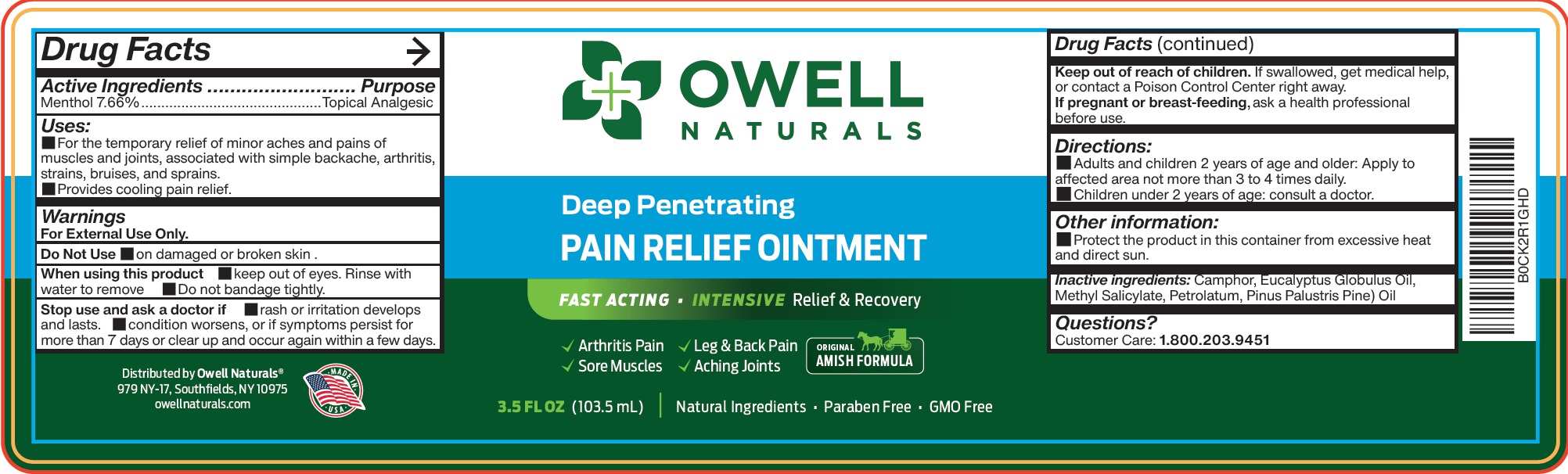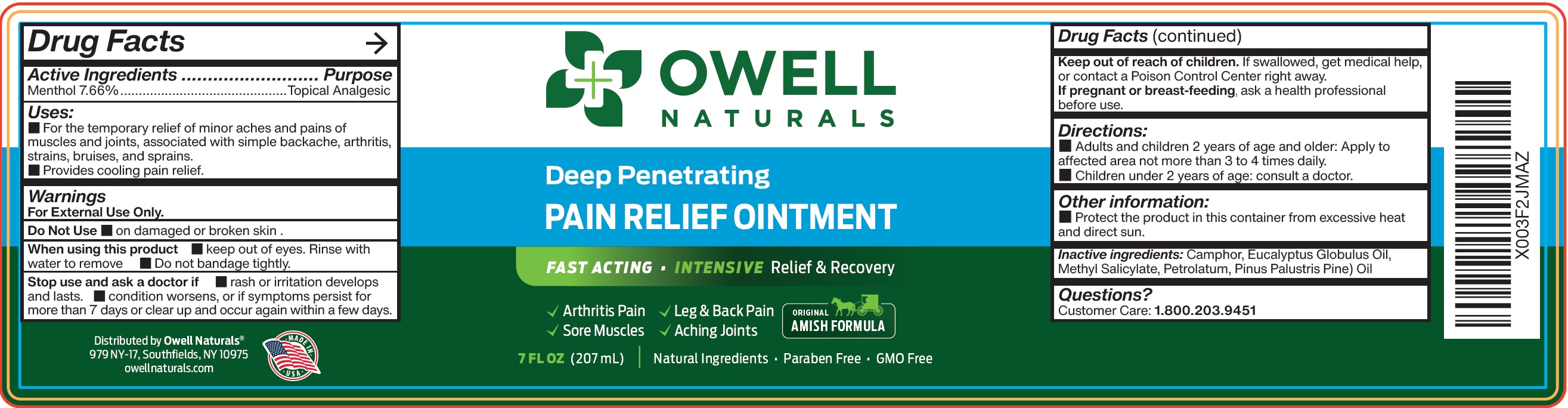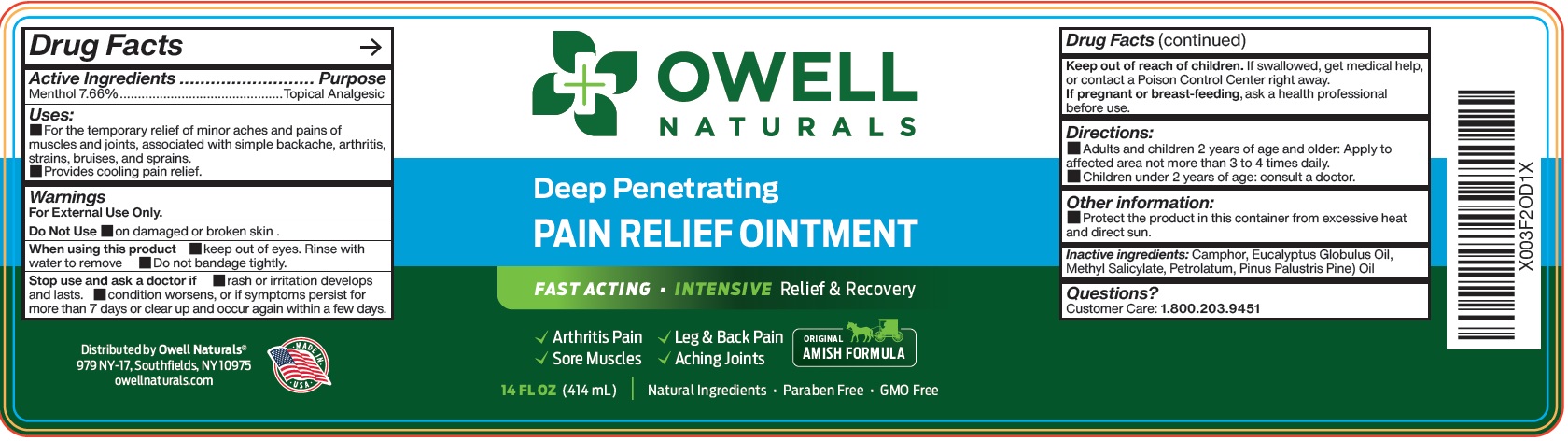 DRUG LABEL: OWELL NATURALS Deep Penetrating Pain Relief
NDC: 83570-443 | Form: OINTMENT
Manufacturer: OWELL NATURALS BRAND, LLC
Category: otc | Type: HUMAN OTC DRUG LABEL
Date: 20240102

ACTIVE INGREDIENTS: MENTHOL 76.6 mg/1 mL
INACTIVE INGREDIENTS: EUCALYPTUS OIL; METHYL SALICYLATE; PETROLATUM

OWELL NATURALS Deep Penetrating Pain Relief Ointment

Active Ingredients

Menthol 7.66%

Purpose

Topical Analgesic

Uses:

- For the temporary relief of minor aches and pains of muscles and joints, associated with simple backache, arthritis, strains, bruises, and sprains.
- Provides cooling pain relief.

Warnings

For External Use Only.

Do Not Use

- on damaged or broken skin.

When using this product

- keep out of eyes. Rinse with water to remove
- Do not bandage tightly.

Stop use and ask a doctor if

- rash or irritation develops and lasts.
- condition worsens, or if symptoms persist for more than 7 days or clear up and occur again within a few days.

Keep out of reach of children.

If swallowed, get medical help, or contact a Poison Control Center right away.

If pregnant or breast-feeding,

ask a health professional before use.

Directions:

- Adults and children 2 years of age and older: Apply to affected area not more than 3 to 4 times daily.
- Children under 2 years of age: consult a doctor.

Other information:

- Protect the product in this container from excessive heat and direct sun.

Inactive ingredients:

Camphor, Eucalyptus Globulus Oil, Methyl Salicylate, Petrolatum, Pinus Palustris Pine) Oil

Questions?

Customer Care: 1.800.203.9451